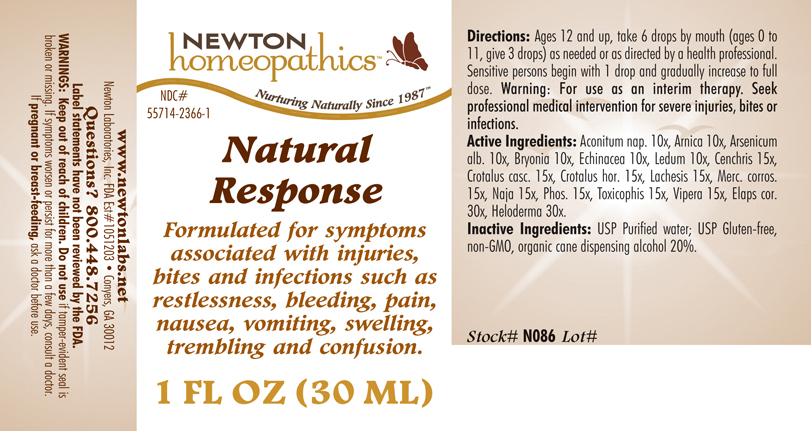 DRUG LABEL: Natural Response 
NDC: 55714-2366 | Form: LIQUID
Manufacturer: Newton Laboratories, Inc.
Category: homeopathic | Type: HUMAN OTC DRUG LABEL
Date: 20141110

ACTIVE INGREDIENTS: Aconitum Napellus 10 [hp_X]/1 mL; Arnica Montana 10 [hp_X]/1 mL; Arsenic Trioxide 10 [hp_X]/1 mL; Bryonia Alba Root 10 [hp_X]/1 mL; Echinacea, Unspecified 10 [hp_X]/1 mL; Ledum Palustre Twig 10 [hp_X]/1 mL; Agkistrodon Contortrix Venom 15 [hp_X]/1 mL; Crotalus Durissus Terrificus Venom 15 [hp_X]/1 mL; Crotalus Horridus Horridus Venom 15 [hp_X]/1 mL; Lachesis Muta Venom 15 [hp_X]/1 mL; Mercuric Chloride 15 [hp_X]/1 mL; Naja Naja Venom 15 [hp_X]/1 mL; Phosphorus 15 [hp_X]/1 mL; Agkistrodon Piscivorus Venom 15 [hp_X]/1 mL; Vipera Berus Venom 15 [hp_X]/1 mL; Micrurus Corallinus Venom 30 [hp_X]/1 mL; Heloderma Suspectum Venom 30 [hp_X]/1 mL
INACTIVE INGREDIENTS: Alcohol; Water

Natural Response

INDICATIONS & USAGE SECTION

Formulated for symptoms associated with injuries, bites and infections such as restlessness, bleeding, pain, nausea, vomiting, swelling, trembling and confusion.

DOSAGE & ADMINISTRATION SECTION

Directions: Ages 12 and up, take 6 drops by mouth (ages 0 to 11, give 3 drops) as needed or as directed by a health professional. Sensitive persons begin with 1 drop and gradually increase to full dose. Warning: For use as an interim therapy. Seek professional medical intervention for severe injuries, bites or infections.

OTC - ACTIVE INGREDIENT SECTION

Aconitum nap. 10x, Arnica 10x, Arsenicum alb. 10x, Bryonia 10x, Echinacea 10x, Ledum 10x, Cenchris 15x, Crotalus casc. 15x, Crotalus hor. 15x, Lachesis 15x, Merc. corros. 15x, Naja 15x, Phos. 15x, Toxicophis 15x, Vipera 15x, Elaps cor. 30x, Heloderma 30x.

OTC - PURPOSE SECTION

Formulated for symptoms associated with injuries, bites and infections such as restlessness, bleeding, pain, nausea, vomiting, swelling, trembling and confusion.

INACTIVE INGREDIENT SECTION

Inactive Ingredients: USP Purified Water; USP Gluten-free, non-GMO, organic cane dispensing alcohol 20%

QUESTIONS SECTION

www.newtonlabs.net Newton Laboratories, Inc. FDA Est # 1051203 - Conyers, GA 30012
Questions? 1.800.448.7256

WARNINGS SECTION

Warning: Keep out of reach of children. Do not use if tamper-evident seal is broken or missing. If symptoms worsen or persist for more than a few days, consult a doctor. If pregnant or breast-feeding, ask a doctor before use.

OTC - PREGNANCY OR BREAST FEEDING SECTION

If pregnant or breast-feeding, ask a doctor before use.

OTC - KEEP OUT OF REACH OF CHILDREN SECTION

Keep out of reach of children.